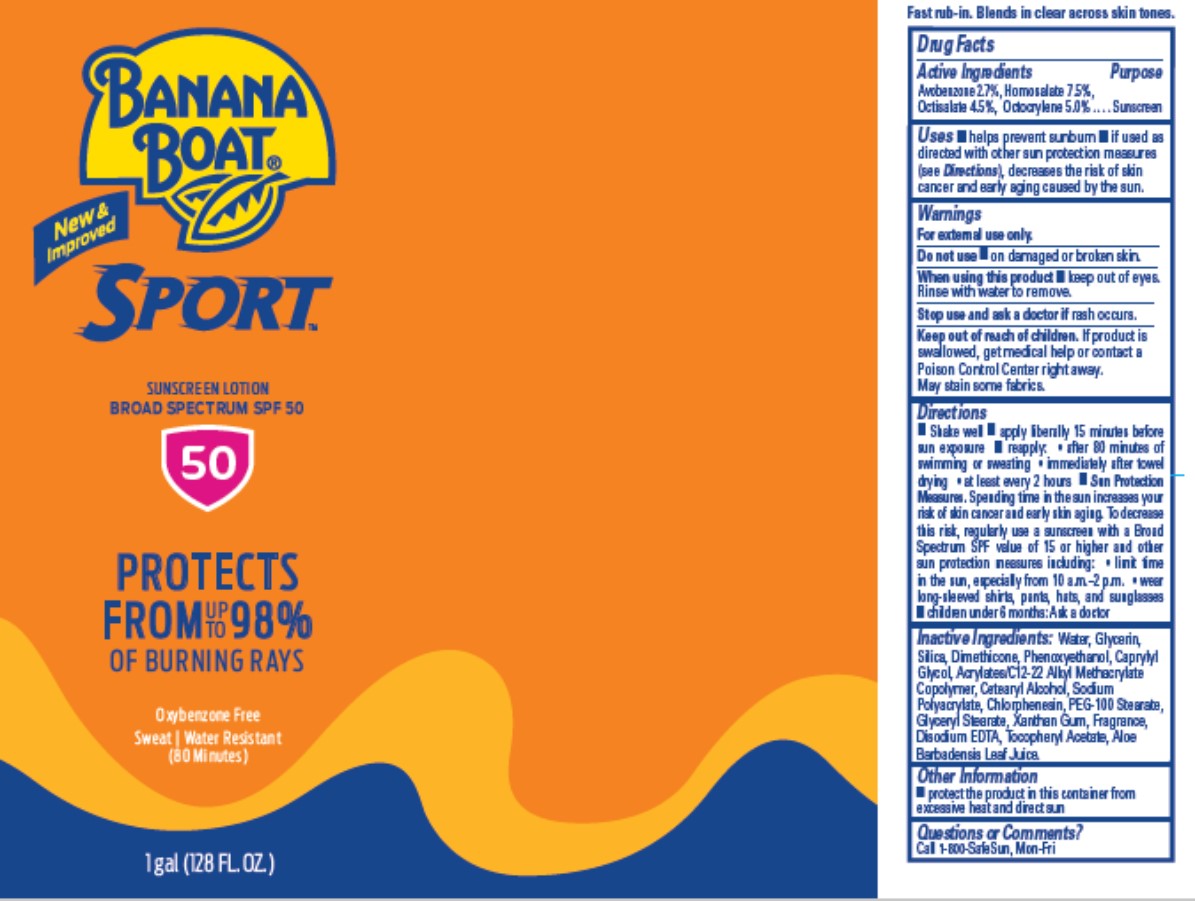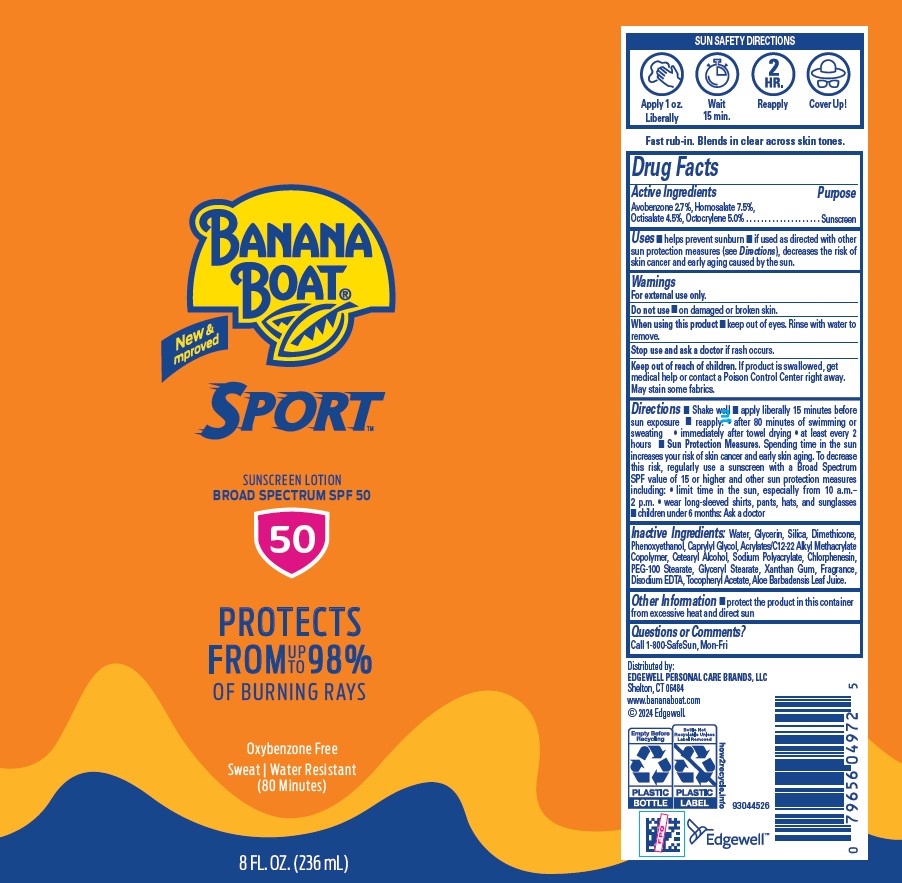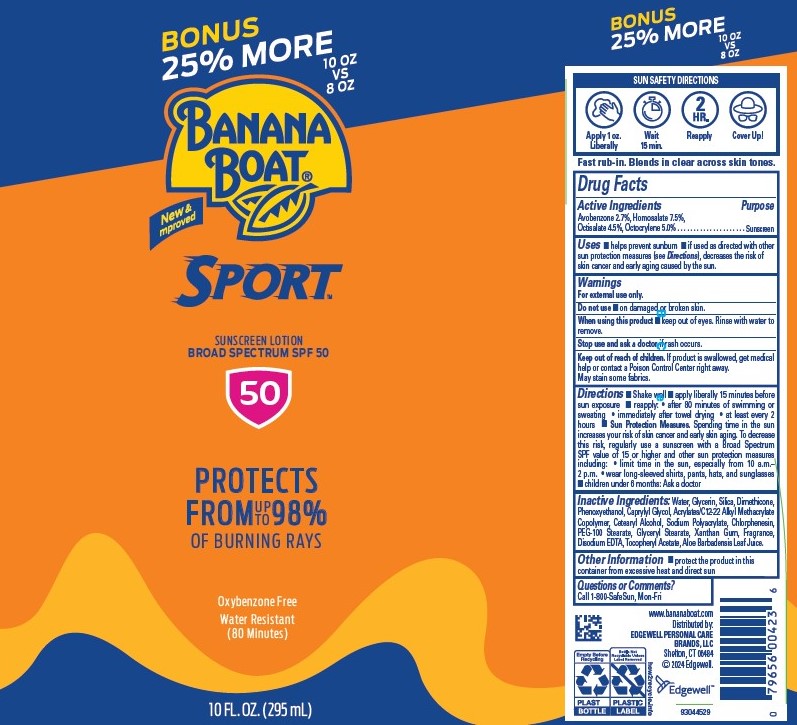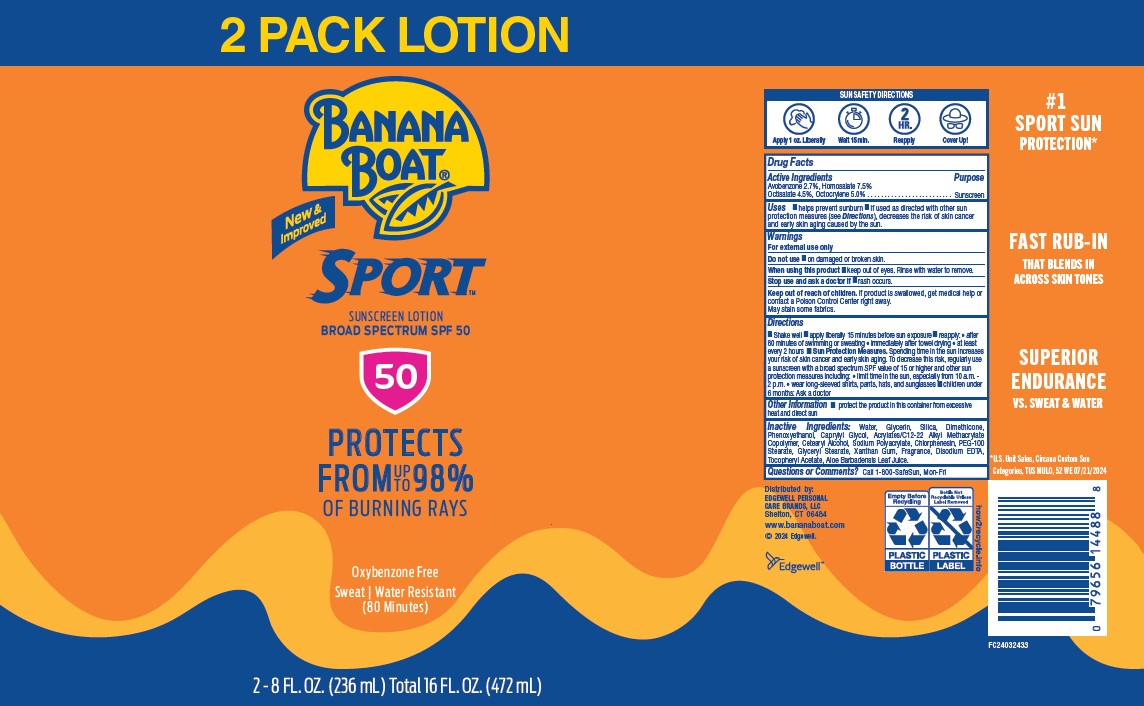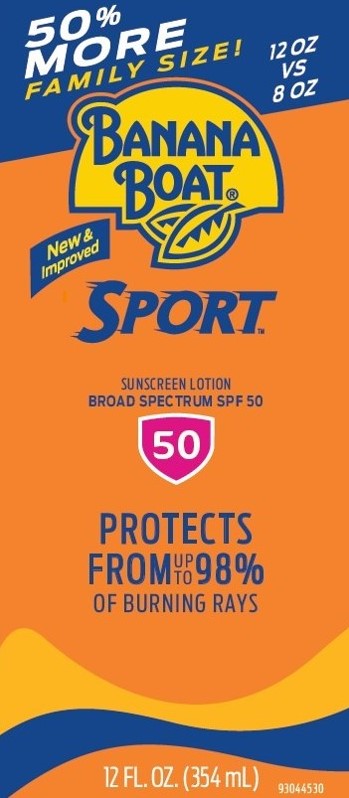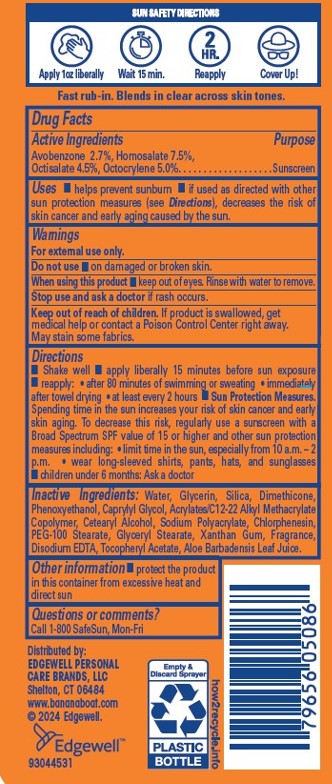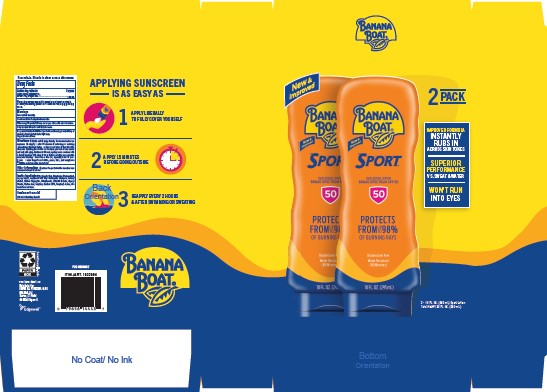 DRUG LABEL: BANANA BOAT
NDC: 63354-141 | Form: LOTION
Manufacturer: Edgewell Personal Care Brands LLC
Category: otc | Type: HUMAN OTC DRUG LABEL
Date: 20251117

ACTIVE INGREDIENTS: OCTOCRYLENE 5 g/100 g; HOMOSALATE 7.5 g/100 g; AVOBENZONE 2.7 g/100 g; OCTISALATE 4.5 g/100 g
INACTIVE INGREDIENTS: SILICON DIOXIDE; PHENOXYETHANOL; WATER; GLYCERYL MONOSTEARATE; SODIUM POLYACRYLATE (2500000 MW); GLYCERIN; DIMETHICONE; CAPRYLYL GLYCOL; CETOSTEARYL ALCOHOL; CHLORPHENESIN; PEG-100 STEARATE; XANTHAN GUM; EDETATE DISODIUM; .ALPHA.-TOCOPHEROL ACETATE; ALOE VERA LEAF

Active Ingredients

Avobenzone 2.7%, Homosalate 7.5%, Octisalate 4.5%, Octocrylene 5.0%.

Purpose

Sunscreen

Uses

• helps prevent sunburn • if used as directed with other sun protection measures (see Directions), decreases the risk of skin cancer and early aging caused by the sun.

Warnings

For external use only.

May stain some fabrics.

Do not use

• on damaged or broken skin.

When using this product

• keep out of eyes. Rinse with water to remove.

Stop use and ask a doctor

if rash occurs.

Keep out of reach of children.

If product is swallowed, get medical help or contact a Poison Control Center right away.

Directions

• Shake well • apply liberally 15 minutes before sun exposure • reapply: • after 80 minutes of swimming or sweating • immediately after towel drying • at least every 2 hours • Sun Protection Measures. Spending time in the sun increases your risk of skin cancer and early skin aging. To decrease this risk, regularly use a sunscreen with a Broad Spectrum SPF value of 15 or higher and other sun protection measures including: • limit time in the sun, especially from 10 a.m. – 2 p.m. • wear long-sleeved shirts, pants, hats, and sunglasses J• children under 6 months: Ask a doctor

Inactive Ingredients:

Water, Glycerin, Silica, Dimethicone, Phenoxyethanol, Caprylyl Glycol, Acrylates/C12-22 Alkyl Methacrylate Copolymer, Cetearyl Alcohol, Sodium Polyacrylate, Chlorphenesin, PEG-100 Stearate, Glyceryl Stearate, Xanthan Gum, Fragrance, Disodium EDTA, Tocopheryl Acetate, Aloe Barbadensis Leaf Juice.

Other information

• protect the product in this container from excessive heat and direct sun

Questions or comments?

Call 1-800 SafeSun, Mon-Fri

PRINCIPAL DISPLAY PANEL

BONUS

25% MORE

10 OZ

VS

8 0Z

BANANA BOAT

New &

Improved

SPORT

SUNSCREEN LOTION

BROAD SPECTRUM SPF 50

50

PROTECTS

FROM UP TO 98%

OF BURNING RAYS

OXYBENZONE FREE

WATER RESISTANT

10 FL. OZ. (295 mL)

BANANA BOAT

New &

Improved

SPORT

SUNSCREEN LOTION

BROAD SPECTRUM SPF 50

50

PROTECTS

FROM UP TO 98%

OF BURNING RAYS

Oxybenzone Free

Sweat | Water Resistant

(80 Minutes)

1 gal (128 FL. OZ.)

BANANA BOAT

New &

Improved

SPORT

SUNSCREEN LOTION

BROAD SPECTRUM SPF 50

50

PROTECTS

FROM UP TO 98%

OF BURNING RAYS

Oxybenzone Free

Sweat | Water Resistant

(80 Minutes)

8 FL. OZ. (236 mL)

50%

MORE

FAMILY SIZE!

12OZ

VS

8OZ

BANANA BOAT

New &

Improved

SPORT

SUNSCREEN LOTION

BROAD SPECTRUM SPF 50

50

PROTECTS

FROM UP TO 98%

OF BURNING RAYS

12 FL OZ. (354 mL)

BANANA BOAT

New &

Improved

2 PACK

IMPROVED FORMULA

INSTANTLY

RUBS IN

ACROSS ALL SKIN TONES

SUPERIOR

PERFORMANCE

VS. SWEAT & WATER

WON'T RUN

INTO EYES

BANANA BOAT

New &

Improved

SPORT

SUNSCREEN LOTION

BROAD SPECTRUM SPF 50

50

PROTECTS

FROM UP TO 98%

OF BURNING RAYS

Oxybenzone Free

Sweat | Water Resistant

(80 Minutes)

2-10 FL.OZ (295 mL)

2 PACK LOTION

BANANA BOAT

New &

Improved

SPORT

SUNSCREEN LOTION

BROAD SPECTRUM SPF 50

50

PROTECTS

FROM UP TO 98%

OF BURNING RAYS

Oxybenzone Free

Sweat | Water Resistant

(80 Minutes)

2-8 FL.OZ (236 mL) TOTAL 16 FL. OZ. (472 mL)